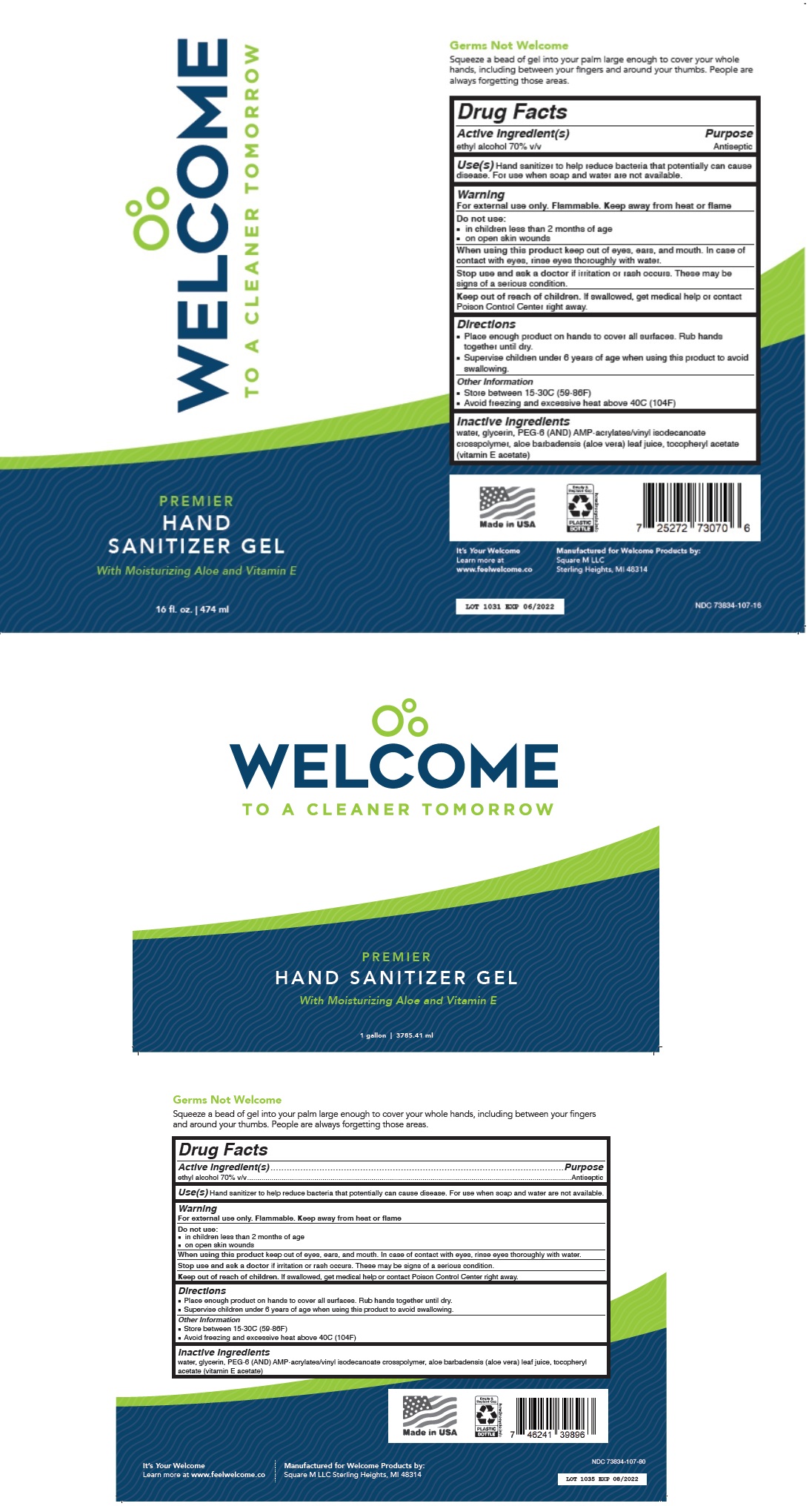 DRUG LABEL: WELCOME
NDC: 73834-107 | Form: GEL
Manufacturer: Square M Llc
Category: otc | Type: HUMAN OTC DRUG LABEL
Date: 20201201

ACTIVE INGREDIENTS: ALCOHOL 70 mL/100 mL
INACTIVE INGREDIENTS: WATER; GLYCERIN; POLYETHYLENE GLYCOL 300; AMINOMETHYLPROPANOL; VINYL NEODECANOATE; ALOE VERA LEAF; .ALPHA.-TOCOPHEROL ACETATE

WELCOME PREMIER HAND SANITIZER GEL

Active Ingredient(s)

ethyl alcohol 70% v/v

Purpose

Antiseptic

INDICATIONS AND USAGE

Use(s) Hand sanitizer to help reduce bacteria that potentially can cause disease. For use when soap and water are not available.

Warning

For external use only. Flammable. Keep away from heat or flame

Do not use:

■ in children less than 2 months of age

■ on open skin wounds

When using this product keep out of eyes, ears, and mouth. In case of contact with eyes, rinse eyes thoroughly with water.

Stop use and ask a doctor if irritation or rash occurs. These may be signs of a serious condition.

Keep out of reach of children. If swallowed, get medical help or contact Poison Control Center right away.

Directions

■ Place enough product on hands to cover all surfaces. Rub hands together until dry.

■ Supervise children under 6 years of age when using this product to avoid swallowing.

Other Information

■ Store between 15-30C (59-86F)

■ Avoid freezing and excessive heat above 40C (104F)

Inactive Ingredients

water, glycerin, PEG-6 (AND) AMP-acrylates/vinyl isodecanoate crosspolymer, aloe barbadensis (aloe vera) leaf juice, tocopheryl acetate (vitamin E acetate)

TO A CLEANER TOMORROW

With Moisturizing Aloe and Vitamin E

Germs Not Welcome

Squeeze a bead of gel into your palm large enough to cover your whole hands, including between your fingers and around your thumbs. People are always forgetting those areas.

Made in USA

It’s Your Welcome
Learn more at
www.feelwelcome.co

Manufactured for Welcome Products by:
Square M LLC
Sterling Heights, MI 48314